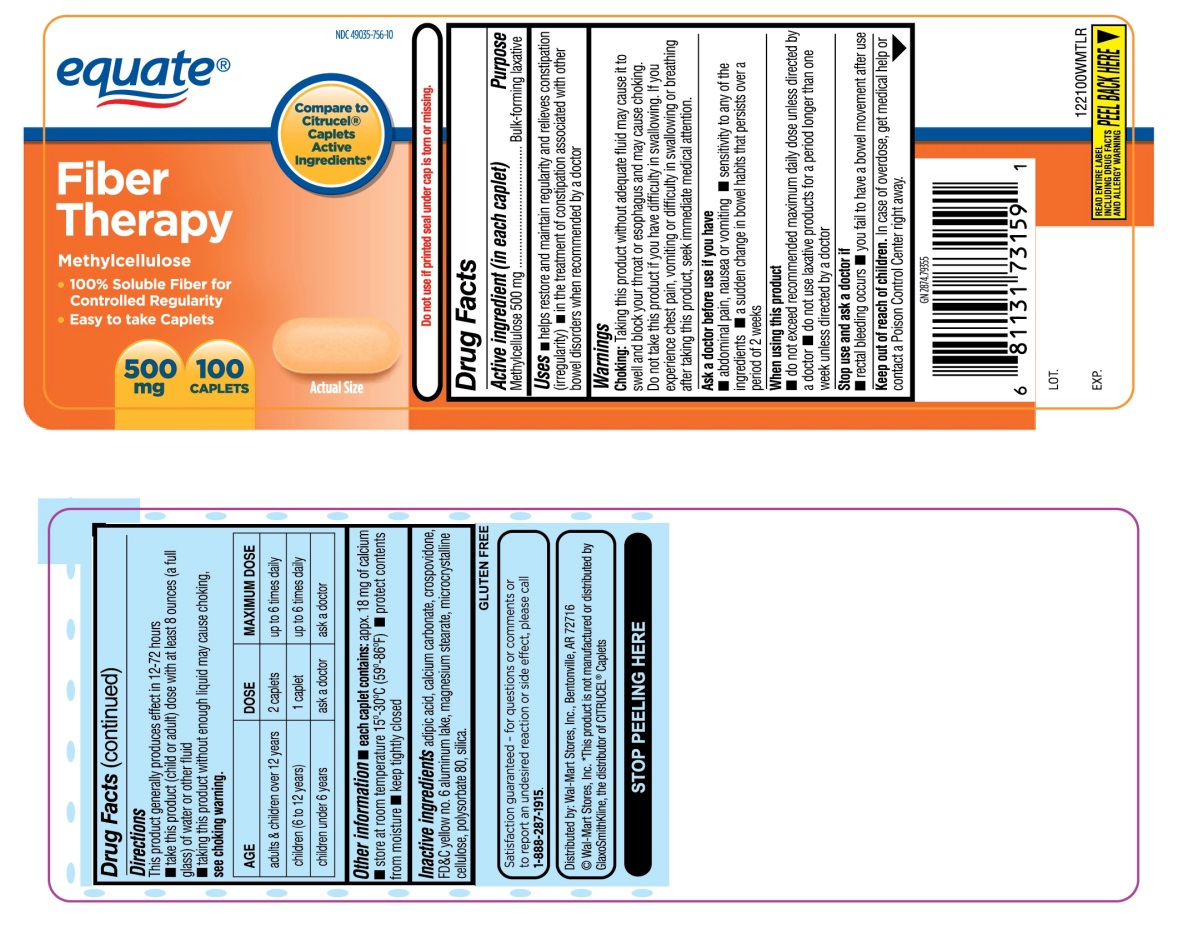 DRUG LABEL: equate Fiber Therapy
NDC: 49035-756 | Form: TABLET
Manufacturer: Wal-Mart Stores,Inc.,
Category: otc | Type: HUMAN OTC DRUG LABEL
Date: 20251027

ACTIVE INGREDIENTS: METHYLCELLULOSE (4000 MPA.S) 500 mg/1 1
INACTIVE INGREDIENTS: ADIPIC ACID; CALCIUM CARBONATE; CROSPOVIDONE (120 .MU.M); FD&C YELLOW NO. 6; MAGNESIUM STEARATE; MICROCRYSTALLINE CELLULOSE; POLYSORBATE 80; SILICON DIOXIDE

equate® Fiber Therapy Methylcellulose 500 mg 100 Caplets

Active ingredient (in each caplet)

Methylcellulose 500 mg

Purpose

Bulk-forming laxative

Uses

- helps restore and maintain regularity and relieves constipation (irregularity)
- in the treatment of constipation associated with other bowel disorders when recommended by a doctor

Warnings

Choking: Taking this product without adequate fluid may cause it to swell and block your throat or esophagus and may cause choking. Do not take this product if you have difficulty in swallowing. If you experience chest pain, vomiting or difficulty in swallowing or breathing after taking this product, seek immediate medical attention.

Ask a doctor before use if you have

- abdominal pain, nausea or vomiting
- sensitivity to any of the ingredients
- a sudden change in bowel habits that persists over a period of 2 weeks

When using this product

- do not exceed recommended maximum daily dose unless directed by a doctor
- do not use laxative products for a period longer than one week unless directed by a doctor

Stop use and ask a doctor if

- rectal bleeding occurs
- you fail to have a bowel movement after use

Keep out of reach of children.

In case of overdose, get medical help or contact a Poison Control Center right away.

Directions

This product generally produces effect in 12-72 hours

- take this product (child or adult) dose with at least 8 ounces (a full glass) of water or other fluid
- taking this product without enough liquid may cause choking.
- See choking warning.

AGE | DOSE | MAXIMUM DOSE
adults & children over 12 years | 2 caplets | up to 6 times daily
children(6 to 12 years) | 1 caplet. | up to 6 times daily
children under 6 years | ask a doctor | ask a doctor

Other information

- each caplet contains: appx. 18 mg of calcium
- store at room temperature 15°-30° C(59°-86° F)
- protect contents from moisture
- keep tightly closed

Inactive ingredients

adipic acid, calcium carbonate, crospovidone, FD&C yellow no. 6 aluminum lake, magnesium stearate, microcrystalline cellulose, polysorbate 80, silica.

Do not use if printed seal under cap is torn or missing.

Principal Display Panel

NDC 49035-756-10

Compare to Citrucel® Caplets Active Ingredients*

equate ®

Fiber Therapy

Methylcellulose

- 100% Soluble Fiber for Controlled Regularity
- Easy to take Caplets
- 500 mg 100 CAPLETS

GLUTEN FREE

Satisfaction guaranteed-for questions or comments or to report an undesired reaction or side effect, please call 1-888-287-1915.

Distributed by:

Wal-Mart Stores, Inc., Bentonville, AR 72716

©Wal-Mart Stores, Inc.

*This product is not manufactured or distributed by GlaxoSmithKline, the distributor of Citrucel® Caplets.